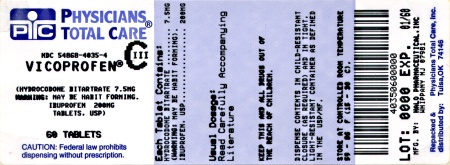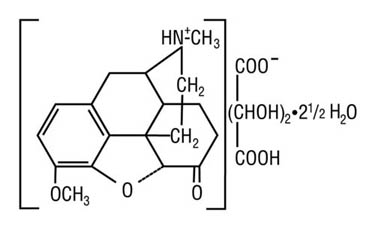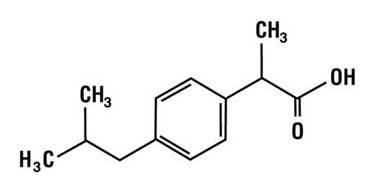 DRUG LABEL: Vicoprofen
NDC: 54868-4035 | Form: TABLET, COATED
Manufacturer: Physicians Total Care, Inc.
Category: prescription | Type: HUMAN PRESCRIPTION DRUG LABEL
Date: 20110812
DEA Schedule: CIII

ACTIVE INGREDIENTS: HYDROCODONE BITARTRATE 7.5 mg/1 1; IBUPROFEN 200 mg/1 1
INACTIVE INGREDIENTS: SILICON DIOXIDE; STARCH, CORN; CROSCARMELLOSE SODIUM; MAGNESIUM STEARATE; CELLULOSE, MICROCRYSTALLINE; POLYETHYLENE GLYCOL; POLYSORBATE 80; TITANIUM DIOXIDE; PROPYLENE GLYCOL; HYPROMELLOSES

VICOPROFEN®
(hydrocodone bitartrate and ibuprofen tablets)
7.5 mg/200 mg
CS-III

DESCRIPTION

Each VICOPROFEN tablet contains:
Hydrocodone Bitartrate, USP 7.5 mg
Ibuprofen, USP 200 mg

VICOPROFEN is supplied in a fixed combination tablet form for oral administration. VICOPROFEN combines the opioid analgesic agent, hydrocodone bitartrate, with the nonsteroidal anti-inflammatory (NSAID) agent, ibuprofen.

Hydrocodone bitartrate is a semisynthetic and centrally acting opioid analgesic. Its chemical name is: 4,5 α-epoxy-3-methoxy-17-methylmorphinan-6-one tartrate (1:1) hydrate (2:5). Its chemical formula is: C18H21NO3•C4H6O6•2½H2O, and the molecular weight is 494.50. Its structural formula is:

Ibuprofen is a nonsteroidal anti-inflammatory agent [non-selective COX inhibitor] with analgesic and antipyretic properties. Its chemical name is: (±)-2-(p-isobutylphenyl) propionic acid. Its chemical formula is: C13H18O2, and the molecular weight is: 206.29. Its structural formula is:

Inactive ingredients in VICOPROFEN tablets include: colloidal silicon dioxide, corn starch, croscarmellose sodium, hypromellose, magnesium stearate, microcrystalline cellulose, polyethylene glycol, polysorbate 80, propylene glycol and titanium dioxide.

CLINICAL PHARMACOLOGY

Hydrocodone Component

Hydrocodone is a semisynthetic opioid analgesic and antitussive with multiple actions qualitatively similar to those of codeine. Most of these involve the central nervous system and smooth muscle. The precise mechanism of action of hydrocodone and other opioids is not known, although it is believed to relate to the existence of opiate receptors in the central nervous system. In addition to analgesia, opioids may produce drowsiness, changes in mood, and mental clouding.

Ibuprofen Component

Ibuprofen is a non-steroidal anti-inflammatory agent that possesses analgesic and antipyretic activities. Its mode of action, like that of other NSAIDs, is not completely understood, but may be related to inhibition of cyclooxygenase activity and prostaglandin synthesis. Ibuprofen is a peripherally acting analgesic. Ibuprofen does not have any known effects on opiate receptors.

Pharmacokinetics

Absorption

After oral dosing with the VICOPROFEN tablet, a peak hydrocodone plasma level of 27 ng/mL is achieved at 1.7 hours, and a peak ibuprofen plasma level of 30 mcg/mL is achieved at 1.8 hours. The effect of food on the absorption of either component from the VICOPROFEN tablet has not been established.

Distribution

Ibuprofen is highly protein-bound (99%) like most other non-steroidal anti-inflammatory agents. Although the extent of protein binding of hydrocodone in human plasma has not been definitely determined, structural similarities to related opioid analgesics suggest that hydrocodone is not extensively protein bound. As most agents in the 5-ring morphinan group of semi-synthetic opioids bind plasma protein to a similar degree (range 19% [hydromorphone] to 45% [oxycodone]), hydrocodone is expected to fall within this range.

Metabolism

Hydrocodone exhibits a complex pattern of metabolism, including O-demethylation, N-demethylation, and 6-keto reduction to the corresponding 6-α-and 6-β-hydroxy metabolites. Hydromorphone, a potent opioid, is formed from the O-demethylation of hydrocodone and contributes to the total analgesic effect of hydrocodone. The O- and N- demethylation processes are mediated by separate P-450 isoenzymes: CYP2D6 and CYP3A4, respectively.

Ibuprofen is present in this product as a racemate, and following absorption it undergoes interconversion in the plasma from the R-isomer to the S-isomer. Both the R- and S- isomers are metabolized to two primary metabolites: (+)-2-4'-(2hydroxy-2-methyl-propyl) phenyl propionic acid and (+)-2-4'-(2carboxypropyl) phenyl propionic acid, both of which circulate in the plasma at low levels relative to the parent.

Elimination

Hydrocodone and its metabolites are eliminated primarily in the kidneys, with a mean plasma half-life of 4.5 hours. Ibuprofen is excreted in the urine, 50% to 60% as metabolites and approximately 15% as unchanged drug and conjugate. The plasma half-life is 2.2 hours.

Special Populations

No significant pharmacokinetic differences based on age or gender have been demonstrated. The pharmacokinetics of hydrocodone and ibuprofen from VICOPROFEN has not been evaluated in children.

Renal Impairment

The effect of renal insufficiency on the pharmacokinetics of the VICOPROFEN dosage form has not been determined.

CLINICAL STUDIES

In single-dose studies of post surgical pain (abdominal, gynecological, orthopedic), 940 patients were studied at doses of one or two tablets. VICOPROFEN produced greater efficacy than placebo and each of its individual components given at the same dose. No advantage was demonstrated for the two-tablet dose.

INDICATIONS AND USAGE

Carefully consider the potential benefits and risks of VICOPROFEN and other treatment options before deciding to use VICOPROFEN. Use the lowest effective dose for the shortest duration consistent with individual patient treatment goals (see WARNINGS).

VICOPROFEN tablets are indicated for the short-term (generally less than 10 days) management of acute pain. VICOPROFEN is not indicated for the treatment of such conditions as osteoarthritis or rheumatoid arthritis.

CONTRAINDICATIONS

VICOPROFEN is contraindicated in patients with known hypersensitivity to hydrocodone or ibuprofen. Patients known to be hypersensitive to other opioids may exhibit cross-sensitivity to hydrocodone.

VICOPROFEN should not be given to patients who have experienced asthma, urticaria, or allergic-type reactions after taking aspirin or other NSAIDs. Severe, rarely fatal, anaphylactic-like reactions to NSAIDs have been reported in such patients (see WARNINGS – Anaphylactoid Reactions, and PRECAUTIONS - Preexisting Asthma).

VICOPROFEN is contraindicated for the treatment of peri-operative pain in the setting of coronary artery bypass graft (CABG) surgery (see WARNINGS).

WARNINGS

CARDIOVASCULAR EFFECTS

Cardiovascular Thrombotic Events

Clinical trials of several COX-2 selective and nonselective NSAIDs of up to three years duration have shown an increased risk of serious cardiovascular (CV) thrombotic events, myocardial infarction, and stroke, which can be fatal. All NSAIDs, both COX-2 selective and nonselective, may have a similar risk. Patients with known CV disease or risk factors for CV disease may be at greater risk. To minimize the potential risk for an adverse CV event in patients treated with an NSAID, the lowest effective dose should be used for the shortest duration possible. Physicians and patients should remain alert for the development of such events, even in the absence of previous CV symptoms. Patients should be informed about the signs and/or symptoms of serious CV events and the steps to take if they occur.

There is no consistent evidence that concurrent use of aspirin mitigates the increased risk of serious CV thrombotic events associated with NSAID use. The concurrent use of aspirin and an NSAID does increase the risk of serious GI events (see GI WARNINGS).

Two large, controlled, clinical trials of a COX-2 selective NSAID for the treatment of pain in the first 10-14 days following CABG surgery found an increased incidence of myocardial infarction and stroke (see CONTRAINDICATIONS).

Hypertension

NSAID-containing products, including VICOPROFEN, can lead to onset of new hypertension or worsening of preexisting hypertension, either of which may contribute to the increased incidence of CV events. Patients taking thiazides or loop diuretics may have impaired response to these therapies when taking NSAIDs. NSAID-containing products, including VICOPROFEN, should be used with caution in patients with hypertension. Blood pressure (BP) should be monitored closely during the initiation of NSAID treatment and throughout the course of therapy.

Congestive Heart Failure and Edema

Fluid retention and edema have been observed in some patients taking NSAIDs. VICOPROFEN should be used with caution in patients with fluid retention or heart failure.

Misuse Abuse and Diversion of Opioids

VICOPROFEN contains hydrocodone an opioid agonist, and is a Schedule III controlled substance. Opioid agonists have the potential for being abused and are sought by abusers and people with addiction disorders, and are subject to diversion.

VICOPROFEN can be abused in a manner similar to other opioid agonists, legal or illicit. This should be considered when prescribing or dispensing VICOPROFEN in situations where the physician or pharmacist is concerned about an increased risk of misuse, abuse or diversion (see DRUG ABUSE AND DEPENDENCE).

Respiratory Depression

At high doses or in opioid-sensitive patients, hydrocodone may produce dose-related respiratory depression by acting directly on the brain stem respiratory centers. Hydrocodone also affects the center that controls respiratory rhythm, and may produce irregular and periodic breathing.

Head Injury and Increased Intracranial Pressure

The respiratory depressant effects of opioids and their capacity to elevate cerebrospinal fluid pressure may be markedly exaggerated in the presence of head injury, intracranial lesions or a pre-existing increase in intracranial pressure. Furthermore, opioids produce adverse reactions, which may obscure the clinical course of patients with head injuries.

Acute Abdominal Conditions

The administration of opioids may obscure the diagnosis or clinical course of patients with acute abdominal conditions.

Gastrointestinal (GI) Effects - Risk of GI Ulceration, Bleeding and Perforation

NSAIDs, including VICOPROFEN, can cause serious gastrointestinal (GI) adverse events including inflammation, bleeding, ulceration, and perforation of the stomach, small intestine, or large intestine, which can be fatal. These serious adverse events can occur at any time, with or without warning symptoms, in patients treated with NSAIDs. Only one in five patients who develops a serious upper GI adverse event on NSAID therapy, is symptomatic. Upper GI ulcers, gross bleeding, or perforation caused by NSAIDs occur in approximately 1% of patients treated for 3-6 months, and in about 2-4% of patients treated for one year. These trends continue with longer duration of use, increasing the likelihood of developing a serious GI event at some time during the course of therapy. However, even short-term therapy is not without risk.

NSAIDs should be prescribed with extreme caution in those with a prior history of ulcer disease or gastrointestinal bleeding. Patients with a prior history of peptic ulcer disease and/or gastrointestinal bleeding who use NSAIDs have a greater than 10-fold increased risk for developing a GI bleed compared to patients with neither of these risk factors. Other factors that increase the risk for GI bleeding in patients treated with NSAIDs include concomitant use of oral corticosteroids or anticoagulants, longer duration of NSAID therapy, smoking, use of alcohol, older age, and poor general health status. Most spontaneous reports of fatal GI events are in elderly or debilitated patients and therefore, special care should be taken in treating this population.

To minimize the potential risk for an adverse GI event in patients treated with an NSAID, the lowest effective dose should be used for the shortest possible duration. Patients and physicians should remain alert for signs and symptoms of GI ulceration and bleeding during NSAID therapy and promptly initiate additional evaluation and treatment if a serious GI adverse event is suspected. This should include discontinuation of the NSAID until a serious GI adverse event is ruled out. For high-risk patients, alternate therapies that do not involve NSAIDs should be considered.

Renal Effects

Long-term administration of NSAIDs has resulted in renal papillary necrosis and other renal injury. Renal toxicity has also been seen in patients in whom renal prostaglandins have a compensatory role in the maintenance of renal perfusion. In these patients, administration of a nonsteroidal anti-inflammatory drug may cause a dose-dependent reduction in prostaglandin formation and, secondarily, in renal blood flow, which may precipitate overt renal decompensation. Patients at greatest risk of this reaction are those with impaired renal function, heart failure, liver dysfunction, those taking diuretics and ACE inhibitors, and the elderly. Discontinuation of NSAID therapy is usually followed by recovery to the pretreatment state.

Advanced Renal Disease

No information is available from controlled clinical studies regarding the use of VICOPROFEN in patients with advanced renal disease. Therefore, treatment with VICOPROFEN is not recommended in patients with advanced renal disease. If VICOPROFEN therapy must be initiated, close monitoring of the patient's renal function is advisable.

Anaphylactoid Reactions

As with other NSAID-containing products, anaphylactoid reactions may occur in patients without known prior exposure to VICOPROFEN. VICOPROFEN should not be given to patients with the aspirin triad. This symptom complex typically occurs in asthmatic patients who experience rhinitis with or without nasal polyps, or who exhibit severe, potentially fatal bronchospasm after taking aspirin or other NSAIDs. Fatal reactions to NSAIDs have been reported in such patients (see CONTRAINDICATIONS and PRECAUTIONS - Pre-existing Asthma). Emergency help should be sought in cases where an anaphylactoid reaction occurs.

Skin Reactions

Products containing NSAIDs, including VICOPROFEN, can cause serious skin adverse events such as exfoliative dermatitis, Stevens-Johnson Syndrome (SJS), and toxic epidermal necrolysis (TEN), which can be fatal. These serious events may occur without warning. Patients should be informed about the signs and symptoms of serious skin manifestations and use of the drug should be discontinued at the first appearance of skin rash or any other sign of hypersensitivity.

Pregnancy

As with other NSAID-containing products, VICOPROFEN should be avoided in late pregnancy because it may cause premature closure of the ductus arteriosus.

PRECAUTIONS

General

VICOPROFEN cannot be expected to substitute for corticosteroids or to treat corticosteroid insufficiency. Abrupt discontinuation of corticosteroids may lead to disease exacerbation. Patients on prolonged corticosteroid therapy should have their therapy tapered slowly if a decision is made to discontinue corticosteroids.

The pharmacological activity of VICOPROFEN in reducing fever and inflammation may diminish the utility of these diagnostic signs in detecting complications of presumed noninfectious, painful conditions.

Special Risk Patients

As with any opioid analgesic agent, VICOPROFEN tablets should be used with caution in elderly or debilitated patients, and those with severe impairment of hepatic or renal function, hypothyroidism, Addison's disease, prostatic hypertrophy or urethral stricture. The usual precautions should be observed and the possibility of respiratory depression should be kept in mind.

Cough Reflex

Hydrocodone suppresses the cough reflex; as with opioids, caution should be exercised when VICOPROFEN is used postoperatively and in patients with pulmonary disease.

Hepatic Effects

Borderline elevations of one or more liver enzymes may occur in up to 15% of patients taking NSAIDs including ibuprofen as found in VICOPROFEN. These laboratory abnormalities may progress, may remain essentially unchanged, or may be transient with continued therapy. Notable elevations of SGPT (ALT) or SGOT (AST) (approximately three or more times the upper limit of normal) have been reported in approximately 1% of patients in clinical trials with NSAIDS. In addition, rare cases of severe hepatic reactions, including jaundice and fatal fulminant hepatitis, liver necrosis and hepatic failure, some of them with fatal outcomes have been reported.

A patient with symptoms and/or signs suggesting liver dysfunction, or in whom an abnormal liver test has occurred, should be evaluated for evidence of the development of more severe hepatic reactions while on VICOPROFEN therapy. If clinical signs and symptoms consistent with liver disease develop, or if systemic manifestations occur (e.g., eosinophilia, rash, etc.), VICOPROFEN should be discontinued.

Hematological Effects

Anemia is sometimes seen in patients receiving NSAIDs including ibuprofen as found in VICOPROFEN. This may be due to fluid retention, occult or gross GI blood loss, or an incompletely described effect upon erythropoiesis. Patients on long-term treatment with NSAIDs including ibuprofen, should have their hemoglobin or hematocrit checked if they exhibit any signs or symptoms of anemia.

NSAIDs inhibit platelet aggregation and have been shown to prolong bleeding time in some patients. Unlike aspirin, their effect on platelet function is quantitatively less, of shorter duration, and reversible. Patients receiving VICOPROFEN who may be adversely affected by alterations in platelet function, such as those with coagulation disorders or patients receiving anticoagulants, should be carefully monitored.

Pre-existing Asthma

Patients with asthma may have aspirin-sensitive asthma. The use of aspirin in patients with aspirin-sensitive asthma has been associated with severe bronchospasm, which may be fatal. Since cross-reactivity between aspirin and other NSAIDs has been reported in such aspirin-sensitive patients, VICOPROFEN should not be administered to patients with this form of aspirin sensitivity and should be used with caution in patients with pre-existing asthma.

Aseptic Meningitis

Aseptic meningitis with fever and coma has been observed on rare occasions in patients on ibuprofen therapy as found in VICOPROFEN. Although it is probably more likely to occur in patients with systemic lupus erythematosus and related connective tissue diseases, it has been reported in patients who do not have an underlying chronic disease. If signs or symptoms of meningitis develop in a patient on VICOPROFEN, the possibility of its being related to ibuprofen should be considered.

Information for Patients

Patients should be informed of the following information before initiating therapy with an NSAID and periodically during the course of ongoing therapy. Patients should also be encouraged to read the NSAID Medication Guide that accompanies each prescription dispensed.

1. VICOPROFEN® (hydrocodone bitartrate 7.5 mg and ibuprofen 200 mg), like other opioid-containing analgesics, may impair mental and/or physical abilities required for the performance of potentially hazardous tasks such as driving a car or operating machinery; patients should be cautioned accordingly.
2. Alcohol and other CNS depressants may produce an additive CNS depression, when taken with this combination product, and should be avoided.
3. VICOPROFEN can be abused in a manner similar to other opioid agonists, legal or illicit. VICOPROFEN may be habit-forming. Patients should take the drug only for as long as it is prescribed, in the amounts prescribed, and no more frequently than prescribed.
4. VICOPROFEN, like other NSAID-containing products, may cause serious CV side effects, such as MI or stroke, which may result in hospitalization and even death. Although serious CV events can occur without warning symptoms, patients should be alert for the signs and symptoms of chest pain, shortness of breath, weakness, slurring of speech, and should ask for medical advice when observing any indicative sign or symptoms. Patients should be apprised of the importance of this follow-up (see WARNINGS, Cardiovascular Effects).
5. VICOPROFEN, like other NSAID-containing products, can cause GI discomfort and serious GI side effects, such as ulcers and bleeding, which may result in hospitalization and even death. Although serious GI tract ulcerations and bleeding can occur without warning symptoms, patients should be alert for the signs and symptoms of ulcerations and bleeding, and should ask for medical advice when observing any indicative sign or symptoms including epigastric pain, dyspepsia, melena, and hematemesis. Patients should be apprised of the importance of this follow-up (see WARNINGS, Gastrointestinal Effects: Risk of Ulceration, Bleeding, and Perforation).
6. VICOPROFEN, like other NSAID-containing products, can cause serious skin side effects such as exfoliative dermatitis, SJS, and TEN, which may result in hospitalizations and even death. Although serious skin reactions may occur without warning, patients should be alert for the signs and symptoms of skin rash and blisters, fever, or other signs of hypersensitivity such as itching, and should ask for medical advice when observing any indicative signs or symptoms. Patients should be advised to stop the drug immediately if they develop any type of rash and contact their physicians as soon as possible.
7. Patients should promptly report signs or symptoms of unexplained weight gain or edema to their physicians.
8. Patients should be informed of the warning signs and symptoms of hepatotoxicity (e.g., nausea, fatigue, lethargy, pruritus, jaundice, right upper quadrant tenderness, and "flu-like" symptoms). If these occur, patients should be instructed to stop therapy and seek immediate medical therapy.
9. Patients should be informed of the signs of an anaphylactoid reaction (e.g., difficulty breathing, swelling of the face or throat). If these occur, patients should be instructed to seek immediate emergency help (see WARNINGS).
10. In late pregnancy, as with other NSAIDs, VICOPROFEN should be avoided because it may cause premature closure of the ductus arteriosus.
11. Patients should be instructed to report any signs of blurred vision or other eye symptoms.

Laboratory Tests

Because serious GI tract ulcerations and bleeding can occur without warning symptoms, physicians should monitor for signs or symptoms of GI bleeding. Patients on long-term treatment with NSAIDs should have their CBC and a chemistry profile checked periodically. If clinical signs and symptoms consistent with liver or renal disease develop, systemic manifestations occur (e.g., eosinophilia, rash, etc.) or if abnormal liver tests persist or worsen, VICOPROFEN should be discontinued.

Drug Interactions

ACE-inhibitors

Reports suggest that NSAIDs may diminish the antihypertensive effect of ACE-inhibitors. This interaction should be given consideration in patients taking VICOPROFEN concomitantly with ACE-inhibitors.

Anticholinergics

The concurrent use of anticholinergics with hydrocodone preparations may produce paralytic ileus.

Antidepressants

The use of Monoamine Oxidase Inhibitors (MAOIs) or tricyclic antidepressants with VICOPROFEN may increase the effect of either the antidepressant or hydrocodone.

MAOIs have been reported to intensify the effects of at least one opioid drug causing anxiety, confusion and significant depression of respiration or coma. The use of hydrocodone is not recommended for patients taking MAOIs or within 14 days of stopping such treatment.

Aspirin

When VICOPROFEN is administered with aspirin, the protein binding of aspirin is reduced, although the clearance of free VICOPROFEN is not altered. The clinical significance of this interaction is not known; however, as with other NSAID-containing products, concomitant administration of VICOPROFEN and aspirin is not generally recommended because of the potential of increased adverse effects.

CNS Depressants

Patients receiving other opioids, antihistamines, antipsychotics, antianxiety agents, or other CNS depressants (including alcohol) concomitantly with VICOPROFEN may exhibit an additive CNS depression. When combined therapy is contemplated, the dose of one or both agents should be reduced.

Diuretics

Ibuprofen has been shown to reduce the natriuretic effect of furosemide and thiazides in some patients. This response has been attributed to inhibition of renal prostaglandin synthesis. During concomitant therapy with VICOPROFEN the patient should be observed closely for signs of renal failure (see WARNINGS - Renal Effects), as well as diuretic efficacy.

Lithium

Ibuprofen has been shown to elevate plasma lithium concentration and reduce renal lithium clearance. The mean minimum lithium concentration increased 15% and the renal clearance was decreased by approximately 20%. This effect has been attributed to inhibition of renal prostaglandin synthesis by ibuprofen. Thus, when VICOPROFEN and lithium are administered concurrently, patients should be observed for signs of lithium toxicity.

Methotrexate

Ibuprofen, as well as other NSAIDs, has been reported to competitively inhibit methotrexate accumulation in rabbit kidney slices. This may indicate that ibuprofen could enhance the toxicity of methotrexate. Caution should be used when VICOPROFEN is administered concomitantly with methotrexate.

Mixed Agonist/Antagonist Opioid Analgesics

Agonist/antagonist analgesics (i.e., pentazocine, nalbuphine, butorphanol and buprenorphine) should be administered with caution to patients who have received or are receiving a course of therapy with a pure opioid agonist analgesic such as hydrocodone. In this situation, mixed agonist/antagonist analgesics may reduce the analgesic effect of hydrocodone and/or may precipitate withdrawal symptoms in these patients.

Neuromuscular Blocking Agents

Hydrocodone, as well as other opioid analgesics, may enhance the neuromuscular blocking action of skeletal muscle relaxants and produce an increased degree of respiratory depression.

Warfarin

The effects of warfarin and NSAIDs on GI bleeding are synergistic, such that users of both drugs together have a risk of serious GI bleeding higher than users of either drug alone.

Carcinogenicity, Mutagenicity, and Impairment of Fertility

The carcinogenic and mutagenic potential of VICOPROFEN has not been investigated. The ability of VICOPROFEN to impair fertility has not been assessed.

Pregnancy

Pregnancy Category C.

Teratogenic Effects

Reproductive studies conducted in rats and rabbits have not demonstrated evidence of developmental abnormalities.

VICOPROFEN, administered to rabbits at 95 mg/kg (5.72 and 1.9 times the maximum clinical dose based on body weight and surface area, respectively), a maternally toxic dose, resulted in an increase in the percentage of litters and fetuses with any major abnormality and an increase in the number of litters and fetuses with one or more nonossified metacarpals (a minor abnormality). VICOPROFEN, administered to rats at 166 mg/kg (10.0 and 1.66 times the maximum clinical dose based on body weight and surface area, respectively), a maternally toxic dose, did not result in any reproductive toxicity. However, animal reproduction studies are not always predictive of human response. There are no adequate and well-controlled studies in pregnant women. VICOPROFEN should be used during pregnancy only if the potential benefit justifies the potential risk to the fetus.

Nonteratogenic Effects

Because of the known effects of nonsteroidal anti-inflammatory drugs on the fetal cardiovascular system (closure of the ductus arteriosus), use during pregnancy (particularly late pregnancy) should be avoided. Babies born to mothers who have been taking opioids regularly prior to delivery will be physically dependent. The withdrawal signs include irritability and excessive crying, tremors, hyperactive reflexes, increased respiratory rate, increased stools, sneezing, yawning, vomiting, and fever. The intensity of the syndrome does not always correlate with the duration of maternal opioid use or dose. There is no consensus on the best method of managing withdrawal.

Labor and Delivery

As with other drugs known to inhibit prostaglandin synthesis, an increased incidence of dystocia and delayed parturition occurred in rats. Administration of VICOPROFEN is not recommended during labor and delivery. The effects of VICOPROFEN on labor and delivery in pregnant women are unknown.

Nursing Mothers

It is not known whether hydrocodone is excreted in human milk. In limited studies, an assay capable of detecting 1 mcg/mL did not demonstrate ibuprofen in the milk of lactating mothers. However, because of the limited nature of the studies, and because of the potential for serious adverse reactions in nursing infants from VICOPROFEN, a decision should be made whether to discontinue nursing or to discontinue the drug, taking into account the importance of the drug to the mother.

Pediatric Use

The safety and effectiveness of VICOPROFEN in pediatric patients below the age of 16 have not been established.

Geriatric Use

In controlled clinical trials there was no difference in tolerability between patients < 65 years of age and those ≥ 65, apart from an increased tendency of the elderly to develop constipation. However, because the elderly may be more sensitive to the renal and gastrointestinal effects of nonsteroidal anti-inflammatory agents as well as possible increased risk of respiratory depression with opioids, extra caution and reduced dosages should be used when treating the elderly with VICOPROFEN.

ADVERSE REACTIONS

VICOPROFEN was administered to approximately 300 pain patients in a safety study that employed dosages and a duration of treatment sufficient to encompass the recommended usage (see DOSAGE AND ADMINISTRATION). Adverse event rates generally increased with increasing daily dose. The event rates reported below are from approximately 150 patients who were in a group that received one tablet of VICOPROFEN an average of three to four times daily. The overall incidence rates of adverse experiences in the trials were fairly similar for this patient group and those who received the comparison treatment, acetaminophen 600 mg with codeine 60 mg.

The following lists adverse events that occurred with an incidence of 1% or greater in clinical trials of VICOPROFEN, without regard to the causal relationship of the events to the drug. To distinguish different rates of occurrence in clinical studies, the adverse events are listed as follows:

name of adverse event = less than 3%

adverse events marked with an asterisk * = 3% to 9%

adverse event rates over 9% are in parentheses.

Body as a Whole

Abdominal pain*; Asthenia*; Fever; Flu syndrome; Headache (27%); Infection*; Pain.

Cardiovascular

Palpitations; Vasodilation.

Central Nervous System

Anxiety*; Confusion; Dizziness (14%); Hypertonia; Insomnia*; Nervousness*; Paresthesia; Somnolence (22%); Thinking abnormalities.

Digestive

Anorexia; Constipation (22%); Diarrhea*; Dry mouth*; Dyspepsia (12%); Flatulence*; Gastritis; Melena; Mouth ulcers; Nausea (21%); Thirst; Vomiting*.

Metabolic and Nutritional Disorders

Edema*.

Respiratory

Dyspnea; Hiccups; Pharyngitis; Rhinitis.

Skin and Appendages

Pruritus*; Sweating*.

Special Senses

Tinnitus.

Urogenital

Urinary frequency.

Incidence less than 1%

Body as a Whole

Allergic reaction.

Cardiovascular

Arrhythmia; Hypotension; Tachycardia.

Central Nervous System

Agitation; Abnormal dreams; Decreased libido; Depression; Euphoria; Mood changes; Neuralgia; Slurred speech; Tremor, Vertigo.

Digestive

Chalky stool; "Clenching teeth"; Dysphagia; Esophageal spasm; Esophagitis; Gastroenteritis; Glossitis; Liver enzyme elevation.

Metabolic and Nutritional

Weight decrease.

Musculoskeletal

Arthralgia; Myalgia.

Respiratory

Asthma; Bronchitis; Hoarseness; Increased cough; Pulmonary congestion; Pneumonia; Shallow breathing; Sinusitis.

Skin and Appendages

Rash; Urticaria.

Special Senses

Altered vision; Bad taste; Dry eyes.

Urogenital

Cystitis; Glycosuria; Impotence; Urinary incontinence; Urinary retention.

DRUG ABUSE AND DEPENDENCE

Misuse Abuse and Diversion of Opioids

VICOPROFEN contains hydrocodone, an opioid agonist, and is a Schedule III controlled substance. VICOPROFEN, and other opioids used in analgesia can be abused and are subject to criminal diversion.

Addiction is a primary, chronic, neurobiologic disease, with genetic, psychosocial, and environmental factors influencing its development and manifestations. It is characterized by behaviors that include one or more of the following: impaired control over drug use, compulsive use, continued use despite harm, and craving. Drug addiction is a treatable disease utilizing a multidisciplinary approach, but relapse is common.

“Drug seeking” behavior is very common in addicts and drug abusers. Drug-seeking tactics include emergency calls or visits near the end of office hours, refusal to undergo appropriate examination, testing or referral, repeated “loss” of prescriptions, tampering with prescriptions and reluctance to provide prior medical records or contact information for other treating physician(s). “Doctor shopping” to obtain additional prescriptions is common among drug abusers and people suffering from untreated addiction.

Abuse and addiction are separate and distinct from physical dependence and tolerance. Physical dependence usually assumes clinically significant dimensions only after several weeks of continued opioid use, although a mild degree of physical dependence may develop after a few days of opioid therapy. Tolerance, in which increasingly large doses are required in order to produce the same degree of analgesia, is manifested initially by a shortened duration of analgesic effect, and subsequently by decreases in the intensity of analgesia. The rate of development of tolerance varies among patients. Physicians should be aware that abuse of opioids can occur in the absence of true addiction and is characterized by misuse for non-medical purposes, often in combination with other psychoactive substances. VICOPROFEN, like other opioids, may be diverted for non-medical use. Record-keeping of prescribing information, including quantity, frequency, and renewal requests is strongly advised.

Proper assessment of the patient, proper prescribing practices, periodic re-evaluation of therapy, and proper dispensing and storage are appropriate measures that help to limit abuse of opioid drugs.

OVERDOSAGE

Following an acute overdosage, toxicity may result from hydrocodone and/or ibuprofen.

Signs and Symptoms

Hydrocodone Component

Serious overdose with hydrocodone is characterized by respiratory depression (a decrease in respiratory rate and/or tidal volume, Cheyne-Stokes respiration, cyanosis) extreme somnolence progressing to stupor or coma, skeletal muscle flaccidity, cold and clammy skin, and sometimes bradycardia and hypotension. In severe overdosage, apnea, circulatory collapse, cardiac arrest and death may occur.

Ibuprofen Component

Symptoms include gastrointestinal irritation with erosion and hemorrhage or perforation, kidney damage, liver damage, heart damage, hemolytic anemia, agranulocytosis, thrombocytopenia, aplastic anemia, and meningitis. Other symptoms may include headache, dizziness, tinnitus, confusion, blurred vision, mental disturbances, skin rash, stomatitis, edema, reduced retinal sensitivity, corneal deposits, and hyperkalemia.

Treatment

Primary attention should be given to the re-establishment of adequate respiratory exchange through provision of a patent airway and the institution of assisted or controlled ventilation. Naloxone, a narcotic antagonist, can reverse respiratory depression and coma associated with opioid overdose or unusual sensitivity to opioids, including hydrocodone. Therefore, an appropriate dose of naloxone hydrochloride should be administered intravenously with simultaneous efforts at respiratory resuscitation. Since the duration of action of hydrocodone may exceed that of the naloxone, the patient should be kept under continuous surveillance and repeated doses of the antagonist should be administered as needed to maintain adequate respiration. Supportive measures should be employed as indicated. Gastric emptying may be useful in removing unabsorbed drug. In cases where consciousness is impaired it may be inadvisable to perform gastric lavage. If gastric lavage is performed, little drug will likely be recovered if more than an hour has elapsed since ingestion. Ibuprofen is acidic and is excreted in the urine; therefore, it may be beneficial to administer alkali and induce diuresis. In addition to supportive measures the use of oral activated charcoal may help to reduce the absorption and reabsorption of ibuprofen. Dialysis is not likely to be effective for removal of ibuprofen because it is very highly bound to plasma proteins.

DOSAGE AND ADMINISTRATION

Carefully consider the potential benefits and risks of VICOPROFEN and other treatment options before deciding to use VICOPROFEN. Use the lowest effective dose for the shortest duration consistent with individual patient treatment goals (see WARNINGS).

After observing the response to initial therapy with VICOPROFEN, the dose and frequency should be adjusted to suit an individual patient's needs.

For the short-term (generally less than 10 days) management of acute pain, the recommended dose of VICOPROFEN is one tablet every 4 to 6 hours, as necessary. Dosage should not exceed 5 tablets in a 24-hour period. It should be kept in mind that tolerance to hydrocodone can develop with continued use and that the incidence of untoward effects is dose related.

The lowest effective dose or the longest dosing interval should be sought for each patient (see WARNINGS), especially in the elderly. After observing the initial response to therapy with VICOPROFEN, the dose and frequency of dosing should be adjusted to suit the individual patient's need, without exceeding the total daily dose recommended.

HOW SUPPLIED

VICOPROFEN tablets are available as:
White film-coated round convex tablets, engraved with "VP" over Abbott "A" logo on one side and plain on the other side.

Bottles of 15 | NDC 54868-4035-3
Bottles of 20 | NDC 54868-4035-1
Bottles of 30 | NDC 54868-4035-0
Bottles of 60 | NDC 54868-4035-4
Bottles of 100 | NDC 54868-4035-2

Storage

Store at 25°C (77°F); excursions permitted to 15°-30°C (59°-86°F). [See USP Controlled Room Temperature].

Dispense in a tight, light-resistant container.

A Schedule CS-III Controlled Substance.

© Abbott

Manufactured by Halo Pharmaceutical Inc.
Whippany, NJ 07981 U.S.A.
for Abbott Laboratories
North Chicago, IL 60064 U.S.A.

Rev. 10/2009

Relabeling and Repackaging by:
Physicians Total Care, Inc.
Tulsa, Oklahoma 74146

Medication Guide
for
Non-Steroidal Anti-Inflammatory Drugs (NSAIDs)
(See the end of this Medication Guide for a list of prescription NSAID medicines.)

What is the most important information I should know about medicines called Non-Steroidal Anti-Inflammatory Drugs (NSAIDs)?

NSAID medicines may increase the chance of a heart attack or stroke that can lead to death.

This chance increases:

- with longer use of NSAID medicines
- in people who have heart disease

NSAID medicines can cause ulcers and bleeding in the stomach and intestines at any time during treatment. Ulcers and bleeding:

- can happen without warning symptoms
- may cause death

The chance of a person getting an ulcer or bleeding increases with:

- taking medicines called “corticosteroids” and “anticoagulants”
- longer use
- smoking
- drinking alcohol
- older age
- having poor health

NSAID medicines should only be used:

- exactly as prescribed
- at the lowest dose possible for your treatment
- for the shortest time needed

What are Non-Steroidal Anti-Inflammatory Drugs (NSAIDs)?

NSAID medicines are used to treat pain and redness, swelling, and heat (inflammation) from medical conditions such as:

- different types of arthritis
- menstrual cramps and other types of short-term pain

Who should not take a Non-Steroidal Anti-Inflammatory Drug (NSAID)?

Do not take an NSAID medicine:

- if you had an asthma attack, hives, or other allergic reaction with aspirin or any other NSAID medicine
- for pain right before or after heart bypass surgery

Tell your healthcare provider:

- about all your medical conditions.
- about all of the medicines you take. NSAIDs and some other medicines can interact with each other and cause serious side effects. Keep a list of your medicines to show to your healthcare provider and pharmacist.
- if you are pregnant. NSAID medicines should not be used by pregnant women late in their pregnancy.
- if you are breastfeeding. Talk to your doctor.

What are the possible side effects of Non-Steroidal Anti-Inflammatory Drugs (NSAIDs)?

Serious side effects include:

- heart attack
- stroke
- high blood pressure
- heart failure from body swelling (fluid retention)
- kidney problems including kidney failure
- bleeding and ulcers in the stomach and intestine
- low red blood cells (anemia)
- life-threatening skin reactions
- life-threatening allergic reactions
- liver problems including liver failure
- asthma attacks in people who have asthma

Other side effects include:

- stomach pain
- constipation
- diarrhea
- gas
- heartburn
- nausea
- vomiting
- dizziness

Get emergency help right away if you have any of the following symptoms:
• shortness of breath or trouble breathing • slurred speech
• chest pain • swelling of the face or throat
• weakness in one part or side of your body

Stop your NSAID medicine and call your healthcare provider right away if you have any of the following symptoms:
• nausea • there is blood in your bowel movement or it is black and sticky like tar
• more tired or weaker than usual • unusual weight gain
• itching • skin rash or blisters with fever
• your skin or eyes look yellow • swelling of the arms and legs, hands and feet
• stomach pain
• flu-like symptoms
• vomit blood

These are not all the side effects with NSAID medicines. Talk to your healthcare provider or pharmacist for more information about NSAID medicines. Call your doctor for medical advice about side effects. You may report side effects to FDA at 1–800–FDA-1088.

Other information about Non-Steroidal Anti-Inflammatory Drugs (NSAIDs)

- Aspirin is an NSAID medicine but it does not increase the chance of a heart attack. Aspirin can cause bleeding in the brain, stomach, and intestines. Aspirin can also cause ulcers in the stomach and intestines.
- Some of these NSAID medicines are sold in lower doses without a prescription (over the counter). Talk to your healthcare provider before using over the counter NSAIDs for more than 10 days.

NSAID medicines that need a prescription

Generic Name | Tradename
Celecoxib | Celebrex
Diclofenac | Cataflam, Voltaren, Arthrotec (combined with misoprostol)
Diflunisal | Dolobid
Etodolac | Lodine, Lodine XL
Fenoprofen | Nalfon, Nalfon 200
Flurbirofen | Ansaid
Ibuprofen | Motrin, Tab-Profen, Vicoprofen* (combined with hydrocodone), Combunox (combined with oxycodone)
Indomethacin | Indocin, Indocin SR, Indo-Lemmon, Indomethagan
Ketoprofen | Oruvail
Ketorolac | Toradol
Mefenamic Acid | Ponstel
Meloxicam | Mobic
Nabumetone | Relafen
Naproxen | Naprosyn, Anaprox, Anaprox DS, EC-Naproxyn, Naprelan, Naprapac (copackaged with lansoprazole)
Oxaprozin | Daypro
Piroxicam | Feldene
Sulindac | Clinoril
Tolmetin | Tolectin, Tolectin DS, Tolectin 600
* Vicoprofen contains the same dose of ibuprofen as over-the-counter (OTC) NSAIDs, and is usually used for less than 10 days to treat pain. The OTC NSAID label warns that long term continuous use may increase the risk of heart attack or stroke.

Manufactured by Halo Pharmaceutical Inc.
Whippany, NJ 07981 U.S.A.
for Abbott Laboratories
North Chicago, IL 60064 U.S.A.

Rev. 10/2009

This Medication Guide has been approved by the U.S. Food and Drug Administration.

PACKAGE LABEL

vicoprofen®

hydrocodone bitartrate and ibuprofen tablets

Each tablet contains:

hydrocodone bitartrate, USP...............7.5 mg

ibuprofen, USP...................................200 mg